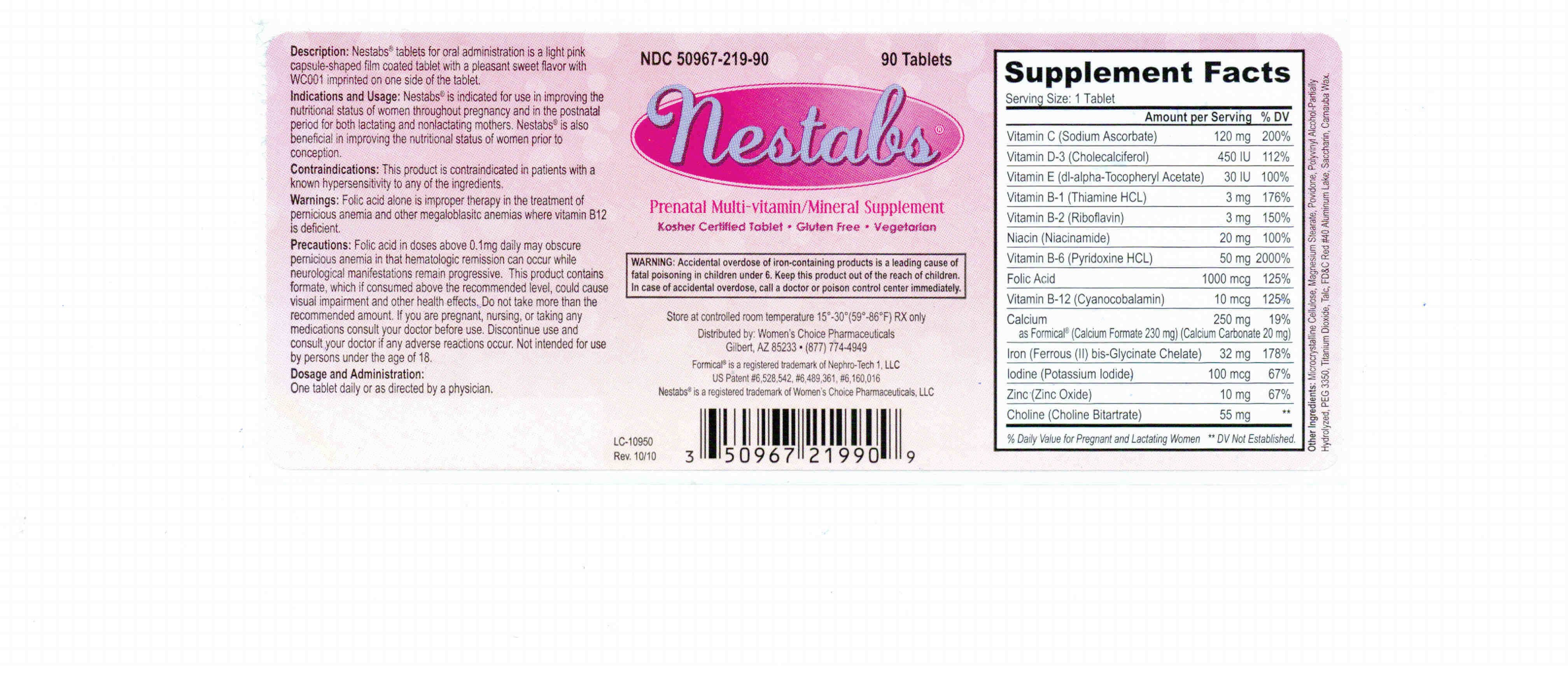 DRUG LABEL: NESTABS
NDC: 50967-219 | Form: TABLET, FILM COATED
Manufacturer: WOMENS CHOICE PHARMACEUTICALS LLC
Category: prescription | Type: HUMAN PRESCRIPTION DRUG LABEL
Date: 20250513

ACTIVE INGREDIENTS: .ALPHA.-TOCOPHEROL ACETATE, D- 30 [iU]/1 1; RIBOFLAVIN 3 mg/1 1; FOLIC ACID 1 mg/1 1; NIACINAMIDE 20 mg/1 1; CYANOCOBALAMIN 10 ug/1 1; POTASSIUM IODIDE 100 ug/1 1; ZINC OXIDE 10 mg/1 1; SODIUM ASCORBATE 120 mg/1 1; THIAMINE MONONITRATE 3 mg/1 1; CHOLECALCIFEROL 450 [iU]/1 1; PYRIDOXINE HYDROCHLORIDE 50 mg/1 1; CALCIUM FORMATE 155 mg/1 1; CALCIUM CARBONATE 45 mg/1 1; FERROUS BISGLYCINATE 32 mg/1 1; CHOLINE BITARTRATE 55 mg/1 1
INACTIVE INGREDIENTS: TITANIUM DIOXIDE; TALC; ALUMINUM OXIDE; CARNAUBA WAX; FD&C RED NO. 40; SACCHARIN; CELLULOSE, MICROCRYSTALLINE; POLYVINYL ALCOHOL, UNSPECIFIED; MAGNESIUM STEARATE; POVIDONE

Nestabs

BOXED WARNING

WARNING: Accidental overdose of iron-containing products is a leading cause of fatal poisoning in children under 6. Keep this product out of the reach of children. In case of accidental overdose, call a doctor or poison control center immediately.

DESCRIPTION

Description: Nestabs tablets for oral administration is a light pink capsule shaped film coated tablet with a pleasant sweet flavor with WC001 imprinted on one side of the tablet.

Indications and Usage: Nestabs is indicated for use in improving the nutritional status of women throughout pregnancy and in the postnatal period for both lactating and nonlactating mothers. Nestabs is also beneficial in improving the nutritional status of women prior to conception.

CONTRAINDICATIONS

Contraindications: This product is contraindicated in patients with a known hypersensitivity to any of the ingredients.

WARNINGS

Warnings: Folic acid alone is improper therapy in the treatment of pernicious anemia and other megaloblastic anemias where vitamin B12 is deficient.

PRECAUTIONS

Precautions: Folic acid in doses above 0.1mg daily may obscure pernicious anemia in that hematologic remission can occur while neurological manifestations remain progressive. This product contains formate, which if consumed above the recommended level, could cause visual impairment and other health effects. Do not take more than the recommended amount. If you are pregnant, nursing, or taking any medications consult your doctor before use. Discontinue use and consult your doctor if any adverse reactions occur. Not intended for use by persons under the age of 18.

Dosage and Administration: One tablet daily or as directed by a physician.